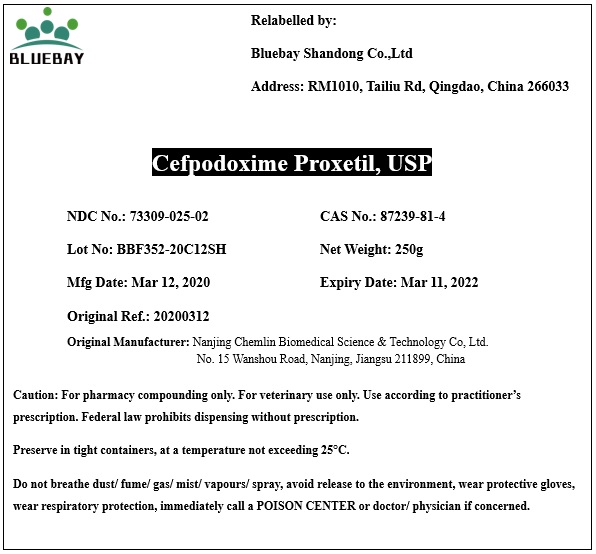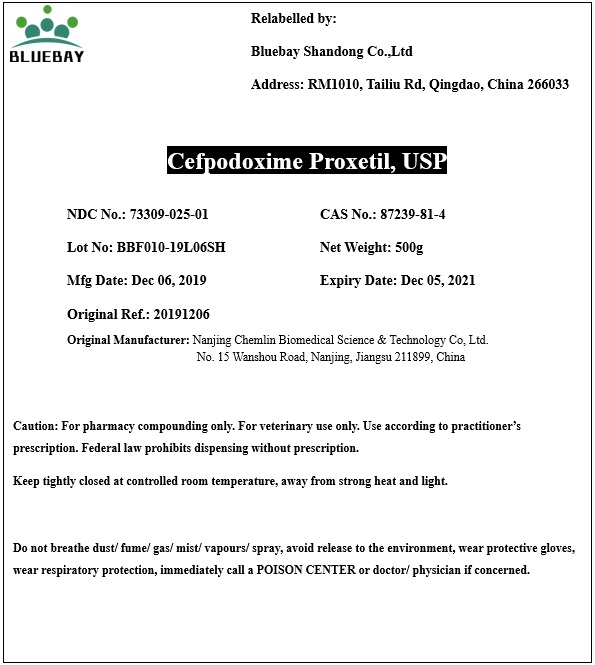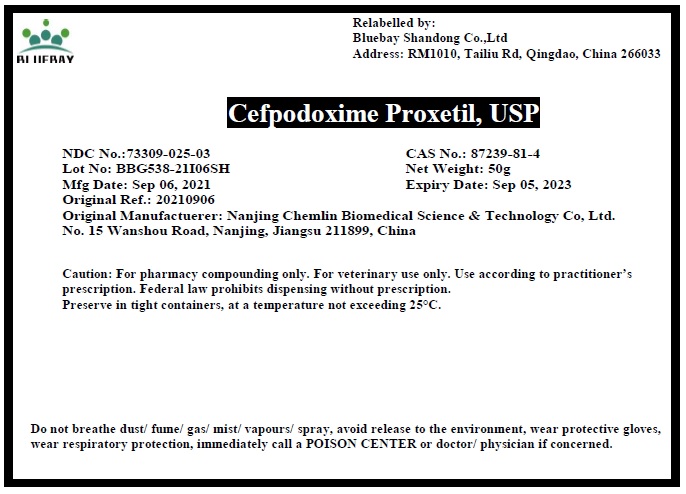 DRUG LABEL: Cefpodoxime Proxetil
NDC: 73309-025 | Form: POWDER
Manufacturer: BLUEBAY SHANDONG CO.,LTD
Category: other | Type: BULK INGREDIENT
Date: 20211028

ACTIVE INGREDIENTS: CEFPODOXIME PROXETIL 1 g/1 g

Cefpodoxime Proxetil